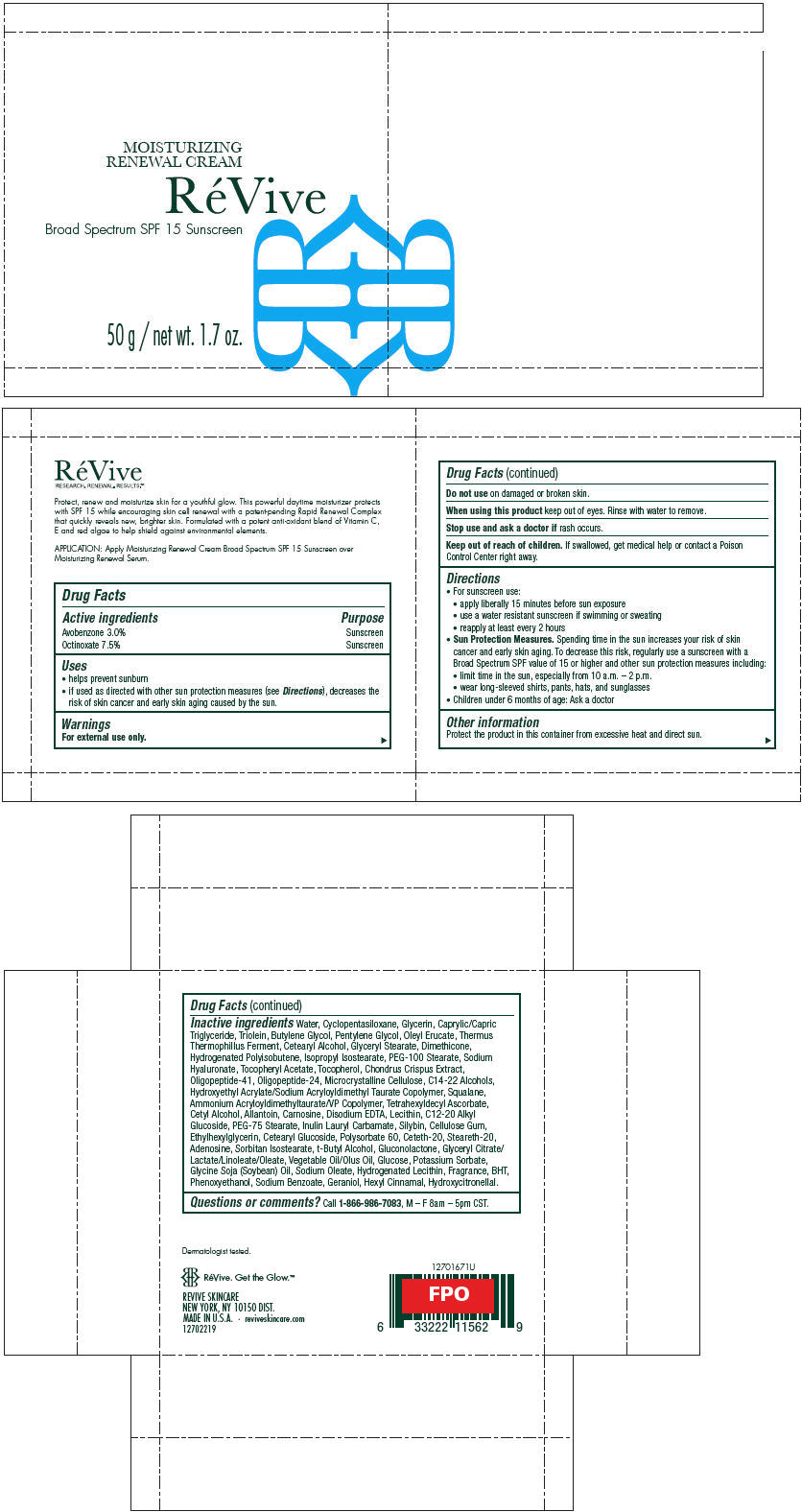 DRUG LABEL: REVIVE MOISTURIZING RENEWAL
NDC: 58411-352 | Form: CREAM
Manufacturer: REVIVE SKINCARE
Category: otc | Type: HUMAN OTC DRUG LABEL
Date: 20171109

ACTIVE INGREDIENTS: AVOBENZONE 1500 mg/50 g; OCTINOXATE 3746 mg/50 g
INACTIVE INGREDIENTS: WATER; Cyclomethicone 5; Glycerin; Medium-Chain Triglycerides; Glyceryl Trioleate; Butylene Glycol; Pentylene Glycol; Oleyl Erucate; Cetostearyl Alcohol; Glyceryl Monostearate; Dimethicone; Hydrogenated Polybutene (1300 Mw); Isopropyl Isostearate; PEG-100 Stearate; Hyaluronate Sodium; .Alpha.-Tocopherol Acetate, DL-; .Alpha.-Tocopherol; Chondrus Crispus Carrageenan; Microcrystalline Cellulose; C14-22 Alcohols; Hydroxyethyl Acrylate/Sodium Acryloyldimethyl Taurate Copolymer (100000 MPA.S at 1.5%); Squalane; Ammonium Acryloyldimethyltaurate/VP Copolymer; Tetrahexyldecyl Ascorbate; Cetyl Alcohol; Allantoin; Carnosine; Edetate Disodium; C12-20 Alkyl Glucoside; PEG-75 Stearate; Silibinin; Carboxymethylcellulose Sodium, Unspecified Form; Ethylhexylglycerin; Cetearyl Glucoside; Polysorbate 60; Ceteth-20; Steareth-20; Adenosine; Sorbitan Isostearate; Tert-Butyl Alcohol; Gluconolactone; Potassium Sorbate; Soybean Oil; Sodium Oleate; BUTYLATED HYDROXYTOLUENE; Phenoxyethanol; Sodium Benzoate; Geraniol; .Alpha.-Hexylcinnamaldehyde; Hydroxycitronellal

RÉVIVE MOISTURIZING RENEWAL CREAM

Drug Facts

ACTIVE INGREDIENT

Active ingredients | Purpose
Avobenzone 3.0% | Sunscreen
Octinoxate 7.5% | Sunscreen

Uses

- helps prevent sunburn
- if used as directed with other sun protection measures (see Directions), decreases the risk of skin cancer and early skin aging caused by the sun.

Warnings

For external use only.

Do not use on damaged or broken skin.

When using this product keep out of eyes. Rinse with water to remove.

Stop use and ask a doctor if rash occurs.

Keep out of reach of children. If swallowed, get medical help or contact a Poison Control Center right away.

Directions

- For sunscreen use:
  - apply liberally 15 minutes before sun exposure
  - use a water resistant sunscreen if swimming or sweating
  - reapply at least every 2 hours
- Sun Protection Measures. Spending time in the sun increases your risk of skin cancer and early skin aging. To decrease this risk, regularly use a sunscreen with a Broad Spectrum SPF value of 15 or higher and other sun protection measures including:
  - limit time in the sun, especially from 10 a.m. – 2 p.m.
  - wear long-sleeved shirts, pants, hats, and sunglasses
- Children under 6 months of age: Ask a doctor

Other information

Protect the product in this container from excessive heat and direct sun.

Inactive ingredients

Water, Cyclopentasiloxane, Glycerin, Caprylic/Capric Triglyceride, Triolein, Butylene Glycol, Pentylene Glycol, Oleyl Erucate, Thermus Thermophillus Ferment, Cetearyl Alcohol, Glyceryl Stearate, Dimethicone, Hydrogenated Polyisobutene, Isopropyl Isostearate, PEG-100 Stearate, Sodium Hyaluronate, Tocopheryl Acetate, Tocopherol, Chondrus Crispus Extract, Oligopeptide-41, Oligopeptide-24, Microcrystalline Cellulose, C14-22 Alcohols, Hydroxyethyl Acrylate/Sodium Acryloyldimethyl Taurate Copolymer, Squalane, Ammonium Acryloyldimethyltaurate/VP Copolymer, Tetrahexyldecyl Ascorbate, Cetyl Alcohol, Allantoin, Carnosine, Disodium EDTA, Lecithin, C12-20 Alkyl Glucoside, PEG-75 Stearate, Inulin Lauryl Carbamate, Silybin, Cellulose Gum, Ethylhexylglycerin, Cetearyl Glucoside, Polysorbate 60, Ceteth-20, Steareth-20, Adenosine, Sorbitan Isostearate, t-Butyl Alcohol, Gluconolactone, Glyceryl Citrate/Lactate/Linoleate/Oleate, Vegetable Oil/Olus Oil, Glucose, Potassium Sorbate, Glycine Soja (Soybean) Oil, Sodium Oleate, Hydrogenated Lecithin, Fragrance, BHT, Phenoxyethanol, Sodium Benzoate, Geraniol, Hexyl Cinnamal, Hydroxycitronellal.

Questions or comments?

Call 1-866-986-7083, M – F 8am – 5pm CST.

PRINCIPAL DISPLAY PANEL - 50 g Jar Carton

MOISTURIZING
RENEWAL CREAM

RéVive

Broad Spectrum SPF 15 Sunscreen

50 g / net wt. 1.7 oz.